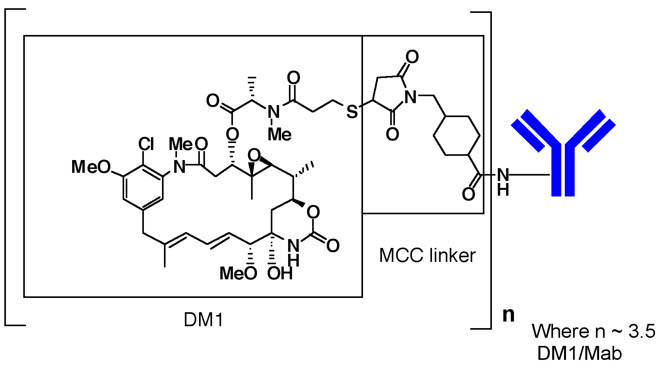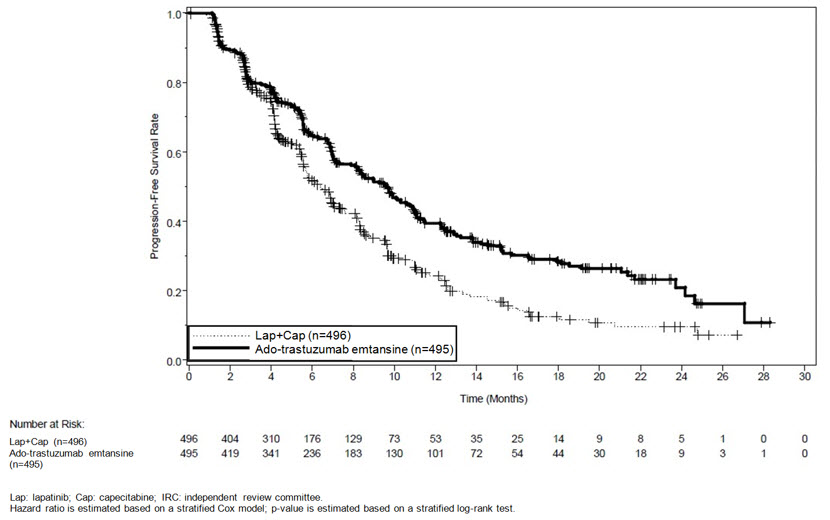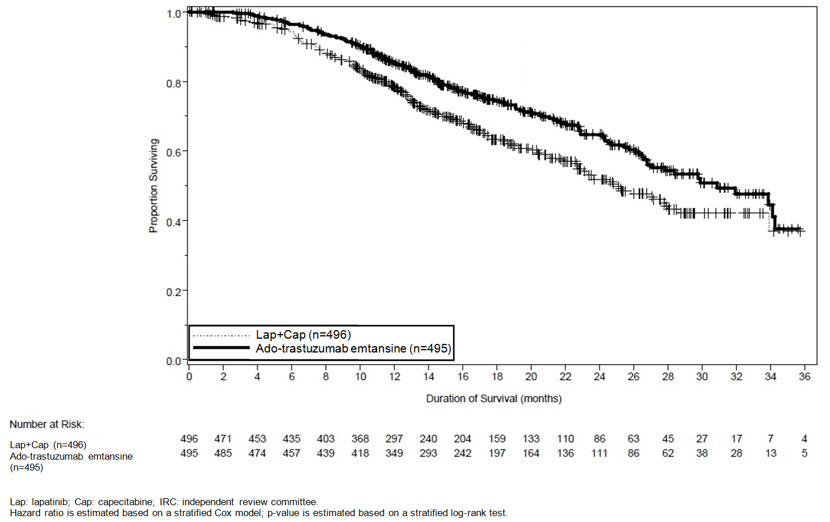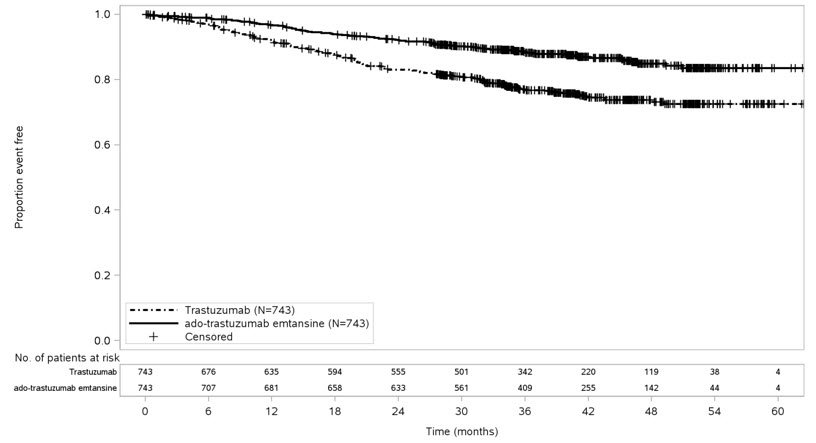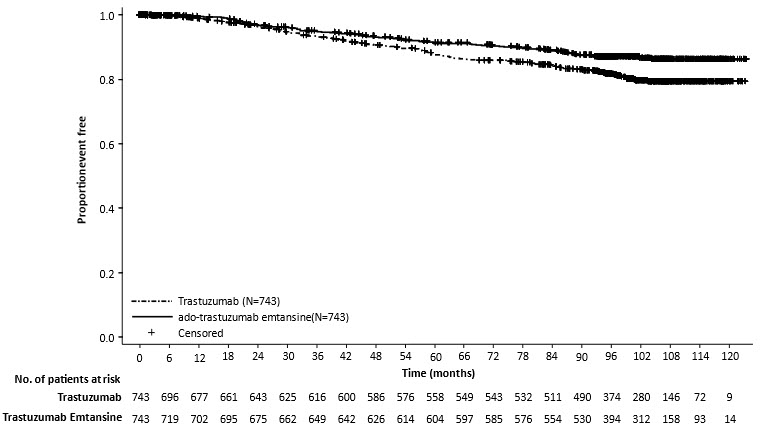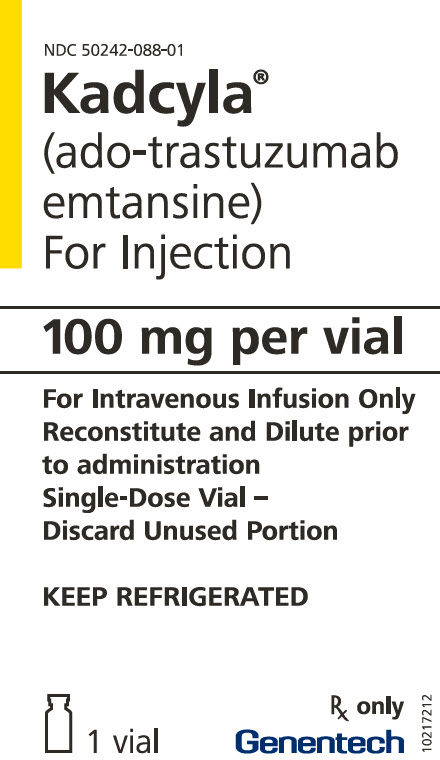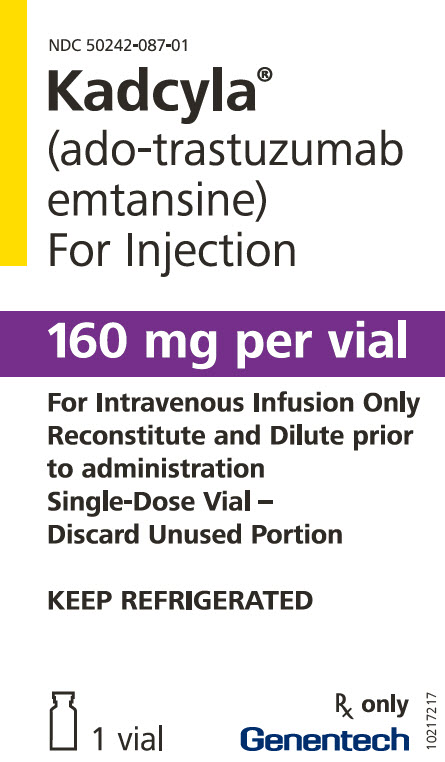 DRUG LABEL: KADCYLA
NDC: 50242-088 | Form: INJECTION, POWDER, LYOPHILIZED, FOR SOLUTION
Manufacturer: Genentech, Inc.
Category: prescription | Type: HUMAN PRESCRIPTION DRUG LABEL
Date: 20251121

ACTIVE INGREDIENTS: TRASTUZUMAB EMTANSINE 20 mg/1 mL
INACTIVE INGREDIENTS: SUCROSE 60 mg/1 mL; SUCCINIC ACID 1.18 mg/1 mL; SODIUM HYDROXIDE 0.45 mg/1 mL; POLYSORBATE 20 0.2 mg/1 mL; WATER

HIGHLIGHTS OF PRESCRIBING INFORMATION

These highlights do not include all the information needed to use KADCYLA safely and effectively. See full prescribing information for KADCYLA.
KADCYLA® (ado-trastuzumab emtansine) for injection, for intravenous use
Initial U.S. Approval: 2013

WARNING: HEPATOTOXICITY, CARDIAC TOXICITY, EMBRYO-FETAL TOXICITY

See full prescribing information for complete boxed warning

- Hepatotoxicity, liver failure and death have occurred in KADCYLA-treated patients. Monitor hepatic function prior to initiation and prior to each dose. Institute dose modifications or permanently discontinue as appropriate. (2.3, 5.1)
- KADCYLA may lead to reductions in left ventricular ejection fraction (LVEF). Assess LVEF prior to initiation. Monitor and withhold dosing or discontinue as appropriate. (2.3, 5.2)
- Embryo-Fetal Toxicity: Exposure to KADCYLA during pregnancy can result in embryo-fetal harm. Advise patients of these risks and the need for effective contraception. (5.3, 8.1, 8.3)

1 INDICATIONS AND USAGE

KADCYLA is a HER2-targeted antibody and microtubule inhibitor conjugate indicated, as a single agent, for:

- the treatment of patients with HER2-positive, metastatic breast cancer who previously received trastuzumab and a taxane, separately or in combination. Patients should have either:
  - received prior therapy for metastatic disease, or
  - developed disease recurrence during or within six months of completing adjuvant therapy. (1.1)
- the adjuvant treatment of patients with HER2-positive early breast cancer who have residual invasive disease after neoadjuvant taxane and trastuzumab-based treatment. (1.2)

Select patients for therapy based on an FDA-approved companion diagnostic for KADCYLA [see Dosage and Administration (2.1)]

2 DOSAGE AND ADMINISTRATION

- Do not substitute KADCYLA for or with trastuzumab.
- HER2 Testing: Perform using FDA-approved tests by laboratories with demonstrated proficiency. (2.1)
- For intravenous infusion only. Do not administer as an intravenous push or bolus. Do not use Dextrose (5%) solution. (2.4)
- The recommended dose of KADCYLA is 3.6 mg/kg given as an intravenous infusion every 3 weeks (21-day cycle) until disease progression or unacceptable toxicity, or a total of 14 cycles for patients with EBC. Do not administer KADCYLA at doses greater than 3.6 mg/kg. (2.2)
- Management of adverse reactions (infusion-related reactions, hepatotoxicity, left ventricular cardiac dysfunction, thrombocytopenia, pulmonary toxicity or peripheral neuropathy) may require temporary interruption, dose reduction, or treatment discontinuation of KADCYLA. (2.3)

3 DOSAGE FORMS AND STRENGTHS

Lyophilized powder in single-dose vials containing 100 mg per vial or 160 mg per vial. (3)

4 CONTRAINDICATIONS

None. (4)

5 WARNINGS AND PRECAUTIONS

- Pulmonary Toxicity: Permanently discontinue KADCYLA in patients diagnosed with interstitial lung disease or pneumonitis. For patients with radiation pneumonitis in the adjuvant setting, permanently discontinue KADCYLA for Grade ≥ 3 or for Grade 2 not responding to standard treatment. (2.2, 5.4)
- Infusion-Related Reactions, Hypersensitivity Reactions: Monitor for signs and symptoms during and after infusion. If significant infusion-related reactions or hypersensitivity reactions occur, slow or interrupt the infusion and administer appropriate medical therapies. Permanently discontinue KADCYLA for life threatening infusion-related reaction. (2.1, 2.2, 5.5)
- Hemorrhage: Fatal cases of hemorrhage occurred in clinical trials among patients with no known identified risk factors, as well as among patients with thrombocytopenia and those receiving anti-coagulation and antiplatelet therapy. Use caution with these agents and consider additional monitoring when concomitant use is medically necessary. (5.6)
- Thrombocytopenia: Monitor platelet counts prior to each KADCYLA dose. Institute dose modifications as appropriate. (2.2, 5.7)
- Neurotoxicity: Monitor for signs or symptoms. Withhold dosing temporarily for patients experiencing Grade 3 or 4 peripheral neuropathy. (2.2, 5.8, 13.2)

6 ADVERSE REACTIONS

Metastatic Breast Cancer

- The most common adverse reactions (≥ 25%) with KADCYLA were fatigue, nausea, musculoskeletal pain, hemorrhage, thrombocytopenia, headache, increased transaminases, constipation and epistaxis. (6.1)

Early Breast Cancer

- The most common adverse reactions (≥ 25%) with KADCYLA were fatigue, nausea, increased transaminases, musculoskeletal pain, hemorrhage, thrombocytopenia, headache, peripheral neuropathy, and arthralgia.

To report SUSPECTED ADVERSE REACTIONS, contact Genentech at 1-888-835-2555 or FDA at 1-800-FDA-1088 or www.fda.gov/medwatch.

8 USE IN SPECIFIC POPULATIONS

- Lactation: Advise not to breastfeed. (8.2)
- Females and Males of Reproductive Potential: Verify pregnancy status of females prior to initiation of KADCYLA. (8.3)

FULL PRESCRIBING INFORMATION

WARNING: HEPATOTOXICITY, CARDIAC TOXICITY, EMBRYO-FETAL TOXICITY

- Hepatotoxicity: Serious hepatotoxicity has been reported, including liver failure and death in patients treated with KADCYLA. Monitor serum transaminases and bilirubin prior to initiation of KADCYLA treatment and prior to each KADCYLA dose. Reduce dose or discontinue KADCYLA as appropriate in cases of increased serum transaminases or total bilirubin. (2.3, 5.1)
- Cardiac Toxicity: KADCYLA administration may lead to reductions in left ventricular ejection fraction (LVEF). Evaluate left ventricular function in all patients prior to and during treatment with KADCYLA. Withhold treatment for clinically significant decrease in left ventricular function. (2.3, 5.2)
- Embryo-Fetal Toxicity: Exposure to KADCYLA during pregnancy can result in embryo-fetal harm. Advise patients of these risks and the need for effective contraception. (5.3, 8.1, 8.3)

1 INDICATIONS AND USAGE

1.1 Metastatic Breast Cancer (MBC)

KADCYLA®, as a single agent, is indicated for the treatment of patients with HER2-positive, metastatic breast cancer who previously received trastuzumab and a taxane, separately or in combination. Patients should have either:

- Received prior therapy for metastatic disease, or
- Developed disease recurrence during or within six months of completing adjuvant therapy.

Select patients for therapy based on an FDA-approved companion diagnostic for KADCYLA [see Dosage and Administration (2.1)].

1.2 Early Breast Cancer (EBC)

KADCYLA, as a single agent, is indicated for the adjuvant treatment of patients with HER2-positive early breast cancer who have residual invasive disease after neoadjuvant taxane and trastuzumab -based treatment.

Select patients for therapy based on an FDA-approved companion diagnostic for KADCYLA [see Dosage and Administration (2.1)].

2 DOSAGE AND ADMINISTRATION

2.1 Patient Selection

Select patients based on HER2 protein overexpression or HER2 gene amplification in tumor specimens [see Indications and Usage (1), Clinical Studies (14)]. Assessment of HER2 protein overexpression and/or HER2 gene amplification should be performed using FDA-approved tests specific for breast cancers by laboratories with demonstrated proficiency. Information on the FDA-approved tests for the detection of HER2 protein overexpression and HER2 gene amplification is available at: http://www.fda.gov/CompanionDiagnostics.

Improper assay performance, including use of sub-optimally fixed tissue, failure to utilize specified reagents, deviation from specific assay instructions, and failure to include appropriate controls for assay validation, can lead to unreliable results.

2.2 Recommended Doses and Schedules

Do not substitute trastuzumab for or with KADCYLA.

The recommended dose of KADCYLA is 3.6 mg/kg given as an intravenous infusion every 3 weeks (21-day cycle). Do not administer KADCYLA at doses greater than 3.6 mg/kg.

Closely monitor the infusion site for possible subcutaneous infiltration during drug administration [see Warnings and Precautions (5.9)].

First infusion: Administer infusion over 90 minutes. Observe patients during the infusion and for at least 90 minutes following the initial dose for fever, chills, or other infusion-related reactions [see Warnings and Precautions (5.5)].

Subsequent infusions: Administer over 30 minutes if prior infusions were well tolerated. Observe patients during the infusion and for at least 30 minutes after infusion.

Metastatic Breast Cancer (MBC)

Patients with MBC should receive treatment until disease progression or unmanageable toxicity.

Early Breast Cancer (EBC)

Patients with EBC should receive treatment for a total of 14 cycles unless there is disease recurrence or unmanageable toxicity.

2.3 Dose Modifications

Do not re-escalate the KADCYLA dose after a dose reduction is made.

If a planned dose is delayed or missed, administer as soon as possible; do not wait until the next planned cycle. Adjust the schedule of administration to maintain a 3-week interval between doses. Administer the infusion at the dose and rate the patient tolerated in the most recent infusion.

Slow or interrupt the infusion rate of KADCYLA if the patient develops an infusion-related reaction. Permanently discontinue KADCYLA for life-threatening infusion-related reactions [see Warnings and Precautions (5.5)].

Management of increased serum transaminases, hyperbilirubinemia, left ventricular dysfunction, thrombocytopenia, pulmonary toxicity or peripheral neuropathy may require temporary interruption, dose reduction or treatment discontinuation of KADCYLA as per guidelines provided in Tables 1 and 2.

Table 1 Recommended Dose Reduction Schedule for Adverse Reactions
Dose Reduction Schedule | Dose Level
Starting dose | 3.6 mg/kg
First dose reduction | 3 mg/kg
Second dose reduction | 2.4 mg/kg
Requirement for further dose reduction | Discontinue treatment

Table 2 Dose Modification Guidelines for KADCYLA
Dose Modifications for Patients with MBC
Adverse reaction | Severity | Treatment modification
Increased Transaminase (AST/ALT) | Grade 2 (> 2.5 to ≤ 5× the ULN) | Treat at the same dose level.
Increased Transaminase (AST/ALT) | Grade 3 (> 5 to ≤ 20× the ULN) | Do not administer KADCYLA until AST/ALT recovers to Grade ≤ 2, and then reduce one dose level
Increased Transaminase (AST/ALT) | Grade 4 (> 20× the ULN) | Discontinue KADCYLA
Hyperbilirubinemia | Grade 2 (> 1.5 to ≤ 3× the ULN) | Do not administer KADCYLA until total bilirubin recovers to Grade ≤ 1, and then treat at the same dose level.
Hyperbilirubinemia | Grade 3 (> 3 to ≤ 10× the ULN) | Do not administer KADCYLA until total bilirubin recovers to Grade ≤ 1 and then reduce one dose level.
Hyperbilirubinemia | Grade 4 (> 10× the ULN) | Discontinue KADCYLA
Drug Induced Liver Injury (DILI) | Serum transaminases > 3 × ULN and concomitant total bilirubin > 2 × ULN | Permanently discontinue KADCYLA in the absence of another likely cause for the elevation of liver enzymes and bilirubin, e.g. liver metastasis or concomitant medication
Nodular Regenerative Hyperplasia (NRH) | All Grades | Permanently discontinue KADCYLA
Thrombocytopenia | Grade 3 (25,000 to < 50,000/mm^3) | Do not administer KADCYLA until platelet count recovers to Grade ≤ 1 (≥ 75,000/mm^3), and then treat at the same dose level
Thrombocytopenia | Grade 4 (< 25,000/mm^3) | Do not administer KADCYLA until platelet count recovers to Grade ≤ 1 (≥ 75,000/mm^3), and then reduce one dose level
Left Ventricular Dysfunction | Symptomatic CHF | Discontinue KADCYLA
Left Ventricular Dysfunction | LVEF < 40% | Do not administer KADCYLA Repeat LVEF assessment within 3 weeks. If LVEF < 40% is confirmed, discontinue KADCYLA
Left Ventricular Dysfunction | LVEF 40% to ≤ 45% and decrease is ≥ 10% points from baseline | Do not administer KADCYLA Repeat LVEF assessment within 3 weeks. If the LVEF has not recovered to within 10% points from baseline, discontinue KADCYLA
Left Ventricular Dysfunction | LVEF 40% to ≤ 45% and decrease is < 10% points from baseline | Continue treatment with KADCYLA. Repeat LVEF assessment within 3 weeks.
Left Ventricular Dysfunction | LVEF > 45% | Continue treatment with KADCYLA.
Pulmonary Toxicity | Interstitial lung disease (ILD) or pneumonitis | Permanently discontinue KADCYLA
Peripheral Neuropathy | Grade 3-4 | Do not administer KADCYLA until resolution Grade ≤ 2
Dose Modification Guidelines for EBC
Adverse reaction | Severity | Treatment modification
Increased Alanine Transaminase (ALT) | Grade 2-3 (> 3.0 to ≤ 20 × ULN on day of scheduled treatment) | Do not administer KADCYLA until ALT recovers to Grade ≤ 1, and then reduce one dose level
Increased Alanine Transaminase (ALT) | Grade 4 (> 20 × ULN at any time) | Discontinue KADCYLA
Increased Aspartate Transaminase (AST) | Grade 2 (> 3.0 to ≤ 5 × ULN on day of scheduled treatment) | Do not administer KADCYLA until AST recovers to Grade ≤ 1, and then treat at the same dose level
Increased Aspartate Transaminase (AST) | Grade 3 (> 5 to ≤ 20 × ULN on day of scheduled treatment) | Do not administer KADCYLA until AST recovers to Grade ≤ 1, and then reduce one dose level
Increased Aspartate Transaminase (AST) | Grade 4 (> 20 × ULN at any time) | Discontinue KADCYLA
Hyperbilirubinemia | TBILI > 1.0 to ≤ 2.0 × the ULN on day of scheduled treatment | Do not administer KADCYLA until total bilirubin recovers to ≤ 1.0 × ULN, and then reduce one dose level
Hyperbilirubinemia | TBILI > 2 × ULN at any time | Discontinue KADCYLA
Nodular Regenerative Hyperplasia (NRH) | All Grades | Permanently discontinue KADCYLA
Thrombocytopenia | Grade 2-3 on day of scheduled treatment (25,000 to < 75,000/mm^3) | Do not administer KADCYLA until platelet count recovers to Grade ≤ 1 (≥ 75,000/mm^3), and then treat at the same dose level. If a patient requires 2 delays due to thrombocytopenia, consider reducing dose by one level.
Thrombocytopenia | Grade 4 at any time < 25,000/mm^3 | Do not administer KADCYLA until platelet count recovers to Grade ≤ 1 (≥ 75,000/mm^3), and then reduce one dose level.
Left Ventricular Dysfunction | LVEF < 45% | Do not administer KADCYLA Repeat LVEF assessment within 3 weeks. If LVEF < 45% is confirmed, discontinue KADCYLA.
Left Ventricular Dysfunction | LVEF 45% to < 50% and decrease is ≥ 10% points from baseline [Prior to starting KADCYLA treatment] | Do not administer KADCYLA Repeat LVEF assessment within 3 weeks. If the LVEF remains < 50% and has not recovered to < 10% points from baseline, discontinue KADCYLA.
Left Ventricular Dysfunction | LVEF 45% to < 50% and decrease is < 10% points from baseline | Continue treatment with KADCYLA. Repeat LVEF assessment within 3 weeks.
Left Ventricular Dysfunction | LVEF ≥ 50% | Continue treatment with KADCYLA.
Heart Failure | Symptomatic CHF, Grade 3-4 LVSD or Grade 3-4 heart failure, or Grade 2 heart failure accompanied by LVEF < 45% | Discontinue KADCYLA
Peripheral Neuropathy | Grade 3-4 | Do not administer KADCYLA until resolution Grade ≤ 2
Pulmonary Toxicity | Interstitial lung disease (ILD) or pneumonitis | Permanently discontinue KADCYLA
Radiotherapy-Related Pneumonitis | Grade 2 | Discontinue KADCYLA if not resolving with standard treatment
Radiotherapy-Related Pneumonitis | Grade 3-4 | Discontinue KADCYLA
ALT = alanine transaminase; AST = aspartate transaminase, CHF = congestive heart failure, DILI = Drug Induced Liver Injury; LVEF = left ventricular ejection fraction, LVSD = left ventricular systolic dysfunction, TBILI = Total Bilirubin, ULN = upper limit of normal

2.4 Preparation for Administration

In order to prevent medication errors it is important to check the vial labels to ensure that the drug being prepared and administered is KADCYLA (ado-trastuzumab emtansine) and not trastuzumab.

Administration:

- Administer KADCYLA as an intravenous infusion only with a 0.2 or 0.22 micron in-line polyethersulfone (PES) filter. Do not administer as an intravenous push or bolus.
- Do not mix KADCYLA, or administer as an infusion, with other medicinal products.

Reconstitution:

- Use aseptic technique for reconstitution and preparation of dosing solution. Appropriate procedures for the preparation of chemotherapeutic drugs should be used.
- Using a sterile syringe, slowly inject 5 mL of Sterile Water for Injection or 0.45% sodium chloride into the 100 mg KADCYLA vial, or 8 mL of Sterile Water for Injection or 0.45% sodium chloride into the 160 mg KADCYLA vial to yield a solution containing 20 mg/mL. Swirl the vial gently until completely dissolved. Do not shake. Inspect the reconstituted solution for particulates and discoloration.
- The reconstituted solution should be clear to slightly opalescent and free of visible particulates. The color of the reconstituted solution should be colorless to pale brown. Do not use if the reconstituted solution contains visible particulates or is cloudy or discolored.
- The reconstituted lyophilized vials should be used immediately following reconstitution with Sterile Water for Injection or 0.45% sodium chloride. If not used immediately, the reconstituted KADCYLA vials can be stored for up to 120 hours (5 days) in a refrigerator at 2ºC to 8ºC (36°F to 46°F); discard unused KADCYLA after 120 hours (5 days) if stored at 2ºC to 8ºC (36°F to 46°F). Do not freeze.
- The reconstituted product contains no preservative and is intended for single-dose only.

Dilution:

Determine the correct dose (mg) of KADCYLA [see Dosage and Administration (2.1)].

- Calculate the volume of the 20 mg/mL reconstituted KADCYLA solution needed.
- Withdraw this amount from the vial and add it to an infusion bag containing 250 mL of 0.9% Sodium Chloride Injection. Do not use Dextrose (5%) solution.
- Gently invert the bag to mix the solution in order to avoid foaming.
- The diluted KADCYLA infusion solution should be used immediately. If not used immediately, the solution may be stored in a refrigerator at 2°C to 8°C (36°F to 46°F) for up to 24 hours prior to use. This storage time is additional to the time allowed for the reconstituted vials. Do not freeze or shake.

3 DOSAGE FORMS AND STRENGTHS

Lyophilized powder in single-dose vials: 100 mg per vial or 160 mg per vial of ado-trastuzumab emtansine.

4 CONTRAINDICATIONS

None.

5 WARNINGS AND PRECAUTIONS

5.1 Hepatotoxicity

Hepatotoxicity, predominantly in the form of asymptomatic, transient increases in the concentrations of serum transaminases, has been observed in clinical trials with KADCYLA [see Adverse Reactions (6.1)]. Serious hepatotoxicity, including 3 fatal cases, has been observed in clinical trials (n=1624) with KADCYLA as single-agent. All fatal cases occurred in MBC clinical trials with KADCYLA, which included severe drug-induced liver injury and associated hepatic encephalopathy. Some of the patients experiencing hepatotoxicity had comorbidities and/or concomitant medications with known hepatotoxic potential.

Monitor serum transaminases and bilirubin prior to initiation of KADCYLA treatment and prior to each KADCYLA dose. Patients with known active liver disease (such as, hepatitis B virus or hepatitis C virus) were excluded from the EMILIA and KATHERINE studies [see Clinical Studies (14.1)]. Reduce the dose or discontinue KADCYLA as appropriate in cases of increased serum transaminases and/or total bilirubin [see Dosage and Administration (2.2)]. Permanently discontinue KADCYLA treatment in patients with serum transaminases > 3 × ULN and concomitant total bilirubin > 2 × ULN. KADCYLA has not been studied in patients with serum transaminases > 2.5 × ULN or bilirubin > 1.5 × ULN prior to the initiation of treatment.

In clinical trials of KADCYLA, cases of nodular regenerative hyperplasia (NRH) of the liver have been identified from liver biopsies (5 cases out of 1624 treated patients, one of which was fatal). Two of these five cases of NRH were observed in EMILIA and two were observed in KATHERINE [see Adverse Reactions (6.1)]. NRH is a rare liver condition characterized by widespread benign transformation of hepatic parenchyma into small regenerative nodules; NRH may lead to non-cirrhotic portal hypertension. The diagnosis of NRH can be confirmed only by histopathology. NRH should be considered in all patients with clinical symptoms of portal hypertension and/or cirrhosis-like pattern seen on the computed tomography (CT) scan of the liver but with normal transaminases and no other manifestations of cirrhosis. Upon diagnosis of NRH, KADCYLA treatment must be permanently discontinued.

5.2 Left Ventricular Dysfunction

Patients treated with KADCYLA are at increased risk of developing left ventricular dysfunction. A decrease of LVEF to < 40% has been observed in patients treated with KADCYLA. Serious cases of heart failure, with no fatal cases, have been observed in clinical trials with KADCYLA. In EMILIA, left ventricular dysfunction occurred in 1.8% of patients in the KADCYLA-treated group and 3.3% of patients in the lapatinib plus capecitabine-treated group. In KATHERINE, left ventricular dysfunction occurred in 0.4% of patients in the KADCYLA-treated group and 0.6% of patients in the trastuzumab-treated group [see Adverse Reactions (6.1)].

Based on limited data from a retrospective observational study, 22% (7 of 32) of patients with HER2-positive metastatic breast cancer (MBC) with a baseline LVEF of 40-49% treated with KADCYLA developed a congestive heart failure (CHF) or a > 10% reduction in LVEF [see Adverse Reactions (6.2)].

Assess LVEF prior to initiation of KADCYLA and at regular intervals (e.g. every three months) during treatment to ensure the LVEF is within the institution's normal limits. KADCYLA has not been studied in an adequately controlled study in patients with LVEF < 50%.

For patients with MBC, if, at routine monitoring, LVEF is < 40%, or is 40% to 45% with a 10% or greater absolute decrease below the pretreatment value, withhold KADCYLA and repeat LVEF assessment within approximately 3 weeks. Permanently discontinue KADCYLA if the LVEF has not improved or has declined further.

For patients with EBC, if, at routine monitoring, LVEF is < 45%, or is 45% to 49% with a 10% or greater absolute decrease below the pretreatment value, withhold KADCYLA and repeat LVEF assessment within approximately 3 weeks. Permanently discontinue KADCYLA if the LVEF has not improved or has declined further [see Dosage and Administration (2.2)].

Patients with a history of symptomatic CHF, serious cardiac arrhythmia, or history of myocardial infarction or unstable angina within 6 months were excluded from the EMILIA and KATHERINE studies [see Clinical Studies (14.1)].

5.3 Embryo-Fetal Toxicity

KADCYLA can cause fetal harm when administered to a pregnant woman. Cases of oligohydramnios, and oligohydramnios sequence manifesting as pulmonary hypoplasia, skeletal abnormalities and neonatal death were observed in the post-marketing setting in patients treated with trastuzumab, the antibody component of KADCYLA. DM1, the cytotoxic component of KADCYLA, can cause embryo-fetal toxicity based on its mechanism of action.

Verify the pregnancy status of females of reproductive potential prior to the initiation of KADCYLA. Advise pregnant women and females of reproductive potential that exposure to KADCYLA during pregnancy or within 7 months prior to conception can result in fetal harm. Advise females of reproductive potential to use effective contraception during treatment and for 7 months following the last dose of KADCYLA [see Use in Specific Populations (8.1, 8.3)].

5.4 Pulmonary Toxicity

Cases of interstitial lung disease (ILD), including pneumonitis, some leading to acute respiratory distress syndrome or fatal outcome have been reported in clinical trials with KADCYLA. Signs and symptoms include dyspnea, cough, fatigue, and pulmonary infiltrates.

In patients with MBC, pneumonitis was reported at an incidence of 0.8% (7 out of 884 treated patients), with one case of Grade 3 pneumonitis. The overall incidence of pneumonitis was 1.2% in EMILIA. In KATHERINE, pneumonitis was reported at an incidence of 1.1% (8 out of 740 patients treated with KADCYLA), with one case of Grade 3 pneumonitis.

Radiation pneumonitis was reported at an incidence of 1.8% (11 out of 623 patients treated with adjuvant radiotherapy and KADCYLA), with 2 cases of Grade 3 radiation pneumonitis [see Adverse Reactions (6.1)].

Permanently discontinue treatment with KADCYLA in patients diagnosed with ILD or pneumonitis. For patients with radiation pneumonitis in the adjuvant setting, KADCYLA should be permanently discontinued for Grade ≥ 3 or for Grade 2 not responding to standard treatment [see Dose Modifications (2.3)].

Patients with dyspnea at rest due to complications of advanced malignancy, co-morbidities, and receiving concurrent pulmonary radiation therapy may be at increased risk of pulmonary toxicity.

5.5 Infusion-Related Reactions, Hypersensitivity Reactions

Treatment with KADCYLA has not been studied in patients who had trastuzumab permanently discontinued due to infusion-related reactions (IRRs) and/or hypersensitivity; treatment with KADCYLA is not recommended for these patients.

Infusion-related reactions, characterized by one or more of the following symptoms − flushing, chills, pyrexia, dyspnea, hypotension, wheezing, bronchospasm, and tachycardia have been reported in clinical trials of KADCYLA. In EMILIA, the overall incidence of IRRs in patients treated with KADCYLA was 1.4%. In KATHERINE, the overall incidence of IRRs in patients treated with KADCYLA was 1.6% [see Adverse Reactions (6.1)]. In most patients, these reactions resolved over the course of several hours to a day after the infusion was terminated. KADCYLA treatment should be interrupted in patients with severe IRR. KADCYLA treatment should be permanently discontinued in the event of a life-threatening IRR [see Dosage and Administration (2.2)]. Patients should be observed closely for IRR reactions, especially during the first infusion.

One case of a serious, allergic/anaphylactic-like reaction has been observed in clinical trials of single-agent KADCYLA. Medications to treat such reactions, as well as emergency equipment, should be available for immediate use.

5.6 Hemorrhage

Cases of hemorrhagic events, including central nervous system, respiratory, and gastrointestinal hemorrhage, have been reported in clinical trials with KADCYLA. Some of these bleeding events resulted in fatal outcomes. In EMILIA, the overall incidence of hemorrhage was 32% in the KADCYLA-treated group and 16% in the lapatinib plus capecitabine-treated group. The incidence of Grade ≥ 3 hemorrhage was 1.8% in the KADCYLA-treated group and 0.8% in the lapatinib plus capecitabine-treated group. In KATHERINE, the overall incidence of hemorrhage was 29% in the KADCYLA-treated group and 10% in the trastuzumab-treated group. The incidence of Grade ≥ 3 hemorrhage was 0.4% in the KADCYLA-treated group, with one fatal case of intracranial hemorrhage, and 0.3% in the trastuzumab-treated group [see Adverse Reactions (6.1)]. Although, in some of the observed cases the patients were also receiving anti-coagulation therapy, antiplatelet therapy, or had thrombocytopenia, in others there were no known additional risk factors. Use caution with these agents and consider additional monitoring when concomitant use is medically necessary.

5.7 Thrombocytopenia

Thrombocytopenia, or decreased platelet count, was reported in clinical trials of KADCYLA (145 of 1624 treated patients with Grade ≥ 3; 494 of 1624 treated patients with any Grade). The majority of these patients had Grade 1 or 2 events (< LLN to ≥ 50,000/mm^3) with the nadir occurring by day 8 and generally improving to Grade 0 or 1 (≥ 75,000/mm^3) by the next scheduled dose. In clinical trials of KADCYLA, the incidence and severity of thrombocytopenia were higher in Asian patients.

In EMILIA, the overall incidence of thrombocytopenia was 31% in the KADCYLA-treated group and 3.3% in the lapatinib plus capecitabine-treated group [see Adverse Reactions (6.1)]. The incidence of Grade ≥ 3 thrombocytopenia was 15% in the KADCYLA-treated group and 0.4% in the lapatinib plus capecitabine-treated group. In Asian patients, the incidence of Grade ≥ 3 thrombocytopenia was 45% in the KADCYLA-treated group and 1.3% in the lapatinib plus capecitabine-treated group.

In KATHERINE, the overall incidence of thrombocytopenia was 29% in the KADCYLA-treated group and 2.4% in the trastuzumab-treated group [see Adverse Reactions (6.1)]. The incidence of Grade ≥ 3 thrombocytopenia was 6% in the KADCYLA-treated group and 0.3% in the trastuzumab-treated group. In Asian patients, the incidence of Grade ≥ 3 thrombocytopenia was 19% in the KADCYLA-treated group and 0% in the trastuzumab-treated group. The overall incidence of thrombocytopenia in the KADCYLA-treated group for Asian patients was 50%.

Monitor platelet counts prior to initiation of KADCYLA and prior to each KADCYLA dose [see Dosage and Administration (2.2)]. KADCYLA has not been studied in patients with platelet counts < 100,000/mm^3 prior to initiation of treatment. In the event of decreased platelet count to Grade ≥ 3 (< 50,000/mm^3) do not administer KADCYLA until platelet counts recover to Grade 1 (≥ 75,000/mm^3) [see Dosage and Administration (2.2)]. Closely monitor patients with thrombocytopenia (< 100,000/mm^3) and patients on anti-coagulant treatment during treatment with KADCYLA.

5.8 Neurotoxicity

Peripheral neuropathy, mainly as Grade 1 and predominantly sensory, was reported in clinical trials of KADCYLA (26 of 1624 treated patients with Grade ≥ 3; 435 of 1624 treated patients with any Grade). In EMILIA, the overall incidence of peripheral neuropathy was 21% in the KADCYLA-treated group and 14% in the lapatinib plus capecitabine-treated group [see Adverse Reactions (6.1)]. The incidence of Grade ≥ 3 peripheral neuropathy was 2.2% in the KADCYLA-treated group and 0.2% in the lapatinib plus capecitabine-treated group. In KATHERINE, the overall incidence of peripheral neuropathy was 32% in the KADCYLA-treated group and 17% in the trastuzumab-treated group. Peripheral neuropathy, including sensory and motor peripheral neuropathy, for KADCYLA treated patients 30% of cases were not resolved at the time of the primary IDFS analysis for KATHERINE. The incidence of Grade ≥ 3 peripheral neuropathy was 1.6% in the KADCYLA-treated group and 0.1% in the trastuzumab-treated group.

KADCYLA should be temporarily discontinued in patients experiencing Grade 3 or 4 peripheral neuropathy until resolution to Grade ≤ 2. Patients should be clinically monitored on an ongoing basis for signs or symptoms of neurotoxicity [see Nonclinical Toxicology (13.2)].

5.9 Extravasation

In KADCYLA clinical studies, reactions secondary to extravasation have been observed. These reactions, observed more frequently within 24 hours of infusion, were usually mild and comprised erythema, tenderness, skin irritation, pain, or swelling at the infusion site. Specific treatment for KADCYLA extravasation is unknown. The infusion site should be closely monitored for possible subcutaneous infiltration during drug administration.

6 ADVERSE REACTIONS

The following adverse reactions are discussed in greater detail in other sections of the label:

- Hepatotoxicity [See Warnings and Precautions (5.1)]
- Left Ventricular Dysfunction [See Warnings and Precautions (5.2)]
- Embryo-Fetal Toxicity [See Warnings and Precautions (5.3)]
- Pulmonary Toxicity [See Warnings and Precautions (5.4)]
- Infusion-Related Reactions, Hypersensitivity Reactions [See Warnings and Precautions (5.5)]
- Hemorrhage [See Warnings and Precautions (5.6)]
- Thrombocytopenia [See Warnings and Precautions (5.7)]
- Neurotoxicity [See Warnings and Precautions (5.8)]

6.1 Clinical Trials Experience

Because clinical trials are conducted under widely varying conditions, adverse reaction rates observed in the clinical trials of a drug cannot be directly compared to rates in the clinical trials of another drug and may not reflect the rates observed in practice.

The data in the WARNINGS AND PRECAUTIONS reflect exposure to KADCYLA as a single agent at 3.6 mg/kg given as an intravenous infusion every 3 weeks (21-day cycle) in 1624 patients including 884 patients with HER2-positive metastatic breast cancer and 740 patients with HER2-positive early breast cancer (KATHERINE trial).

Metastatic Breast Cancer

In clinical trials, KADCYLA has been evaluated as single-agent in 884 patients with HER2-positive metastatic breast cancer. The most common (≥ 25%) adverse reactions were fatigue, nausea, musculoskeletal pain, hemorrhage, thrombocytopenia, headache, increased transaminases, constipation and epistaxis.

The adverse reactions described in Table 3 were identified in patients with HER2-positive metastatic breast cancer treated in the EMILIA trial [see Clinical Studies (14.1)]. Patients were randomized to receive KADCYLA or lapatinib plus capecitabine. The median duration of study treatment was 7.6 months for patients in the KADCYLA-treated group and 5.5 months and 5.3 months for patients treated with lapatinib and capecitabine, respectively.

In the EMILIA trial, 43% of patients experienced Grade ≥ 3 adverse reactions in the KADCYLA-treated group compared with 59% of patients in the lapatinib plus capecitabine-treated group.

Dose adjustments for KADCYLA were permitted [see Dosage and Administration (2.2)]. Thirty-two patients (7%) discontinued KADCYLA due to an adverse reaction, compared with 41 patients (8%) who discontinued lapatinib, and 51 patients (10%) who discontinued capecitabine due to an adverse reaction. The most common adverse reactions leading to KADCYLA discontinuation were thrombocytopenia and increased transaminases. Eighty patients (16%) treated with KADCYLA had adverse reactions leading to dose reductions. The most frequent adverse reactions leading to dose reduction of KADCYLA (in ≥ 1% of patients) included thrombocytopenia, increased transaminases, and peripheral neuropathy. Adverse reactions that led to dose delays occurred in 116 (24%) of KADCYLA treated patients. The most frequent adverse reactions leading to a dose delay of KADCYLA (in ≥ 1% of patients) were neutropenia, thrombocytopenia, leukopenia, fatigue, increased transaminases and pyrexia.

Table 3 reports the adverse reactions that occurred in patients in the KADCYLA-treated group (n=490) of the EMILIA trial. Selected laboratory abnormalities are shown in Table 4. The most common adverse reactions seen with KADCYLA in the randomized trial (frequency > 25%) were nausea, fatigue, musculoskeletal pain, hemorrhage, thrombocytopenia, increased transaminases, headache, and constipation. The most common NCI–CTCAE (version 3) Grade ≥ 3 adverse reactions (frequency > 2%) were thrombocytopenia, increased transaminases, anemia, hypokalemia, peripheral neuropathy and fatigue.

Table 3 Adverse Reactions Occurring in ≥ 10% of Patients on the KADCYLA Treatment Arm in the EMILIA Trial [Grouped terms were used for the following Adverse Reactions: Thrombocytopenia: thrombocytopenia, platelet count decreased Anemia: anemia, hemoglobin decreased Abdominal pain: abdominal pain, abdominal pain upper Stomatitis: stomatitis, mucosal inflammation, oropharyngeal pain Transaminases Increased: transaminases increased, aspartate aminotransferase increased, alanine aminotransferase increased, gamma-glutamyltransferase increased, liver function test abnormal, hepatic enzyme increased, hepatic function abnormal Hypokalemia: hypokalemia, blood potassium decreased Musculoskeletal Pain: muscle spasms, musculoskeletal discomfort, musculoskeletal chest pain, back pain, pain in extremity, bone pain, musculoskeletal pain Peripheral neuropathy: neuropathy peripheral, peripheral sensory neuropathy, peripheral motor neuropathy, paresthesia Hemorrhage: Hemorrhage terms (excl laboratory terms) (SMQ, wide), Hemorrhage laboratory terms (SMQ, narrow).]
Adverse Reactions | KADCYLA (3.6 mg/kg) n=490 |  | Lapatinib (1250 mg) + Capecitabine (2000 mg/m^2) n=488
 | All Grades (%) | Grade 3 – 4 (%) | All Grades (%) | Grade 3 – 4 (%)
Blood and Lymphatic System Disorders
Thrombocytopenia | 31 | 15 | 3.3 | 0.4
Anemia | 14 | 4.1 | 11 | 2.5
Gastrointestinal Disorders
Nausea | 40 | 0.8 | 45 | 2.5
Constipation | 27 | 0.4 | 11 | 0
Diarrhea | 24 | 1.6 | 80 | 21
Vomiting | 19 | 0.8 | 30 | 4.5
Abdominal pain | 19 | 0.8 | 18 | 1.6
Dry Mouth | 17 | 0 | 4.9 | 0.2
Stomatitis | 14 | 0.2 | 33 | 2.5
General Disorders and Administration
Fatigue | 36 | 2.5 | 28 | 3.5
Pyrexia | 19 | 0.2 | 8 | 0.4
Asthenia | 18 | 0.4 | 18 | 1.6
Investigations
Transaminases increased | 29 | 8.0 | 14 | 2.5
Metabolism and Nutrition Disorders
Hypokalemia | 10 | 2.7 | 9 | 4.7
Musculoskeletal and Connective Tissue Disorders
Musculoskeletal pain | 36 | 1.8 | 31 | 1.4
Arthralgia | 19 | 0.6 | 8 | 0
Myalgia | 14 | 0.6 | 3.7 | 0
Nervous System Disorders
Headache | 28 | 0.8 | 15 | 0.8
Peripheral neuropathy | 21 | 2.2 | 14 | 0.2
Dizziness | 10 | 0.4 | 11 | 0.2
Psychiatric Disorders
Insomnia | 12 | 0.4 | 9 | 0.2
Respiratory, Thoracic, and Mediastinal Disorders
Epistaxis | 23 | 0.2 | 8 | 0
Cough | 18 | 0.2 | 13 | 0.2
Dyspnea | 12 | 0.8 | 8 | 0.4
Skin and Subcutaneous Tissue Disorders
Rash | 12 | 0 | 28 | 1.8
Vascular Disorders
Hemorrhage | 32 | 1.8 | 16 | 0.8
SMQ=standardized MedDRA queries

The following clinically relevant adverse reactions were reported in < 10% of patients in the KADCYLA-treated group in EMILIA: dyspepsia (9%), urinary tract infection (9%), chills (8%), dysgeusia (8%), neutropenia (7%), peripheral edema (7%), pruritus (6%), hypertension (5%), blood alkaline phosphatase increased (4.7%), vision blurred (4.5%), conjunctivitis (3.9%), dry eye (3.9%), lacrimation increased (3.3%), drug hypersensitivity (2.2%), left ventricular dysfunction (1.8%), infusion-related reaction (1.4%), pneumonitis (1.2%), nodular regenerative hyperplasia (0.4%), portal hypertension (0.4%).

Table 4 Selected Laboratory Abnormalities (EMILIA)
Parameter | KADCYLA (3.6 mg/kg) |  |  | Lapatinib (1250 mg) + Capecitabine (2000 mg/m^2)
Parameter | All Grades (%) | Grade 3 (%) | Grade 4 (%) | All Grades (%) | Grade 3 (%) | Grade 4 (%)
Chemistry
Increased AST | 98 | 7 | 0.5 | 65 | 3 | 0
Increased ALT | 82 | 5 | 0.2 | 54 | 3 | 0
Decreased potassium | 33 | 3 | 0 | 31 | 6 | 0.8
Increased bilirubin | 17 | 0.6 | 0 | 57 | 2 | 0
Hematology
Decreased platelet count | 83 | 14 | 3 | 21 | 0.4 | 0.6
Decreased hemoglobin | 60 | 4 | 1 | 64 | 3 | 0.2
Decreased neutrophils | 39 | 3 | 0.6 | 38 | 6 | 2

Early Breast Cancer

KADCYLA has been evaluated as a single-agent in 740 patients with HER2-positive early breast cancer.

The adverse reactions described in Table 5 were identified in patients with HER2-positive early breast cancer treated in the KATHERINE trial [see Clinical Studies (14.2)]. Patients were randomized to receive KADCYLA or trastuzumab. The median duration of study treatment was 10 months for patients in the KADCYLA-treated group and 10 months for patients treated with trastuzumab.

One hundred and ninety (26%) patients experienced Grade ≥ 3 adverse reactions in the KADCYLA-treated group compared with 111 (15%) patients in the trastuzumab group. One hundred and thirty-three patients (18%) discontinued KADCYLA due to an adverse reaction, compared with 15 patients (2.1%) who discontinued trastuzumab due to an adverse reaction.

The most common adverse reactions leading to KADCYLA discontinuation (in ≥ 1% of patients) were platelet count decreased, blood bilirubin increased, ejection fraction decreased, AST increased, ALT increased, and peripheral neuropathy.

Dose adjustments for KADCYLA were permitted [see Dosage and Administration (2.2)]. One hundred and six patients (14%) treated with KADCYLA had dose reductions. The most frequent adverse reactions leading to dose reduction of KADCYLA (in ≥ 1% of patients) included thrombocytopenia, increased transaminases, blood bilirubin and fatigue. Adverse reactions that led to dose delays occurred in 106 (14%) of KADCYLA treated patients. The most frequent adverse reactions leading to a dose delay of KADCYLA (in ≥ 1% of patients) were neutropenia, thrombocytopenia and AST increased.

Selected laboratory abnormalities are shown in Table 6. The most common adverse reactions seen with KADCYLA in the randomized trial (frequency > 25%) were fatigue, nausea, increased transaminases, musculoskeletal pain, hemorrhage, thrombocytopenia, headache, peripheral neuropathy, and arthralgia. The most common NCI–CTCAE (version 3) Grade ≥ 3 adverse reactions (> 2%) were thrombocytopenia and hypertension.

Table 5 Adverse Reactions Occurring in ≥ 10% of Patients in the KATHERINE Trial [Grouped terms were used for the following Adverse Reactions: Thrombocytopenia: thrombocytopenia, platelet count decreased Anemia: anemia, hemoglobin decreased Stomatitis: stomatitis, mucosal inflammation, oropharyngeal pain Abdominal pain: abdominal pain, abdominal pain upper Urinary Tract Infection: urinary tract infection, cystitis Transaminases Increased: transaminases increased, aspartate aminotransferase increased, alanine aminotransferase increased, gamma-glutamyltransferase increased, liver function test abnormal, hepatic enzyme increased, hepatic function abnormal Musculoskeletal Pain: muscle spasms, musculoskeletal discomfort, musculoskeletal chest pain, back pain, pain in extremity, bone pain, musculoskeletal pain Peripheral neuropathy: neuropathy peripheral, peripheral sensory neuropathy, peripheral motor neuropathy, paresthesia Hemorrhage: Hemorrhage terms (excl laboratory terms) (SMQ, wide), Hemorrhage laboratory terms (SMQ, narrow)]
Adverse Reactions | KADCYLA n=740 |  | Trastuzumab n=720
 | All grades (%) | Grade 3 – 4 (%) | All grades (%) | Grade 3 – 4 (%)
Blood and Lymphatic System Disorders
Thrombocytopenia | 29 | 6 | 2.4 | 0.3
Anemia | 10 | 1.1 | 9 | 0.1
Gastrointestinal Disorders
Nausea | 42 | 0.5 | 13 | 0.3
Constipation | 17 | 0.1 | 8 | 0
Stomatitis | 15 | 0.1 | 8 | 0.1
Vomiting | 15 | 0.5 | 5 | 0.3
Dry Mouth | 14 | 0.1 | 1.3 | 0
Diarrhea | 12 | 0.8 | 13 | 0.3
Abdominal pain | 11 | 0.4 | 7 | 0.3
General Disorders and Administration
Fatigue | 50 | 1.1 | 34 | 0.1
Pyrexia | 10 | 0 | 4 | 0
Infections and Infestations
Urinary tract infection | 10 | 0.3 | 6 | 0.1
Investigations
Transaminases increased | 32 | 1.5 | 8 | 0.4
Musculoskeletal and Connective Tissue Disorders
Musculoskeletal pain | 30 | 0.7 | 29 | 0.7
Arthralgia | 26 | 0.1 | 21 | 0
Myalgia | 15 | 0.4 | 11 | 0
Nervous System Disorders
Headache | 28 | 0 | 17 | 0.1
Peripheral neuropathy | 28 | 1.6 | 14 | 0.1
Dizziness | 10 | 0.1 | 8 | 0.3
Psychiatric Disorders
Insomnia | 14 | 0 | 12 | 0.1
Respiratory, Thoracic, and Mediastinal Disorders
Epistaxis | 22 | 0 | 3.5 | 0
Cough | 14 | 0.1 | 12 | 0
Vascular Disorders
Hemorrhage | 29 | 0.4 [Included one fatal hemorrhage.] | 10 | 0.3
SMQ=standardized MedDRA queries

The following clinically relevant adverse reactions were reported in < 10% of patients in the KADCYLA-treated group in KATHERINE: blood alkaline phosphatase increased (8%), dysgeusia (8%), dyspnea (8%), neutropenia (8%), blood bilirubin increased (7%), hypokalemia (7%), pruritus (7%), hypertension (6%), lacrimation increased (6%), chills (5%), dry eye (4.5%), dyspepsia (4.3%), peripheral edema (3.9%),vision blurred (3.9%), conjunctivitis (3.5%), left ventricular dysfunction (3.0%), drug hypersensitivity (2.7%), infusion-related reaction (1.6%), radiation pneumonitis (1.5%), pneumonitis (1.1%), rash (1.1%), asthenia (0.4%), nodular regenerative hyperplasia (0.3%).

Table 6 Selected Laboratory Abnormalities (KATHERINE)
Parameter | KADCYLA n=740 |  |  | Trastuzumab n=720
Parameter | All Grade (%) | Grade 3 (%) | Grade 4 (%) | All Grade (%) | Grade 3 (%) | Grade 4 (%)
Chemistry
Increased AST | 79 | 0.8 | 0 | 21 | 0.1 | 0
Increased ALT | 55 | 0.7 | 0 | 21 | 0.1 | 0
Decreased potassium | 26 | 2 | 0.5 | 9 | 0.7 | 0.1
Increased bilirubin | 12 | 0 | 0 | 4 | 0.7 | 0
Hematology
Decreased platelet count | 51 | 4 | 2 | 13 | 0.1 | 0.1
Decreased hemoglobin | 31 | 1 | 0 | 29 | 0.3 | 0
Decreased neutrophils | 24 | 1 | 0 | 19 | 0.6 | 0.6

6.2 Post-Marketing Experience

The following adverse reactions have been identified during post-approval use of KADCYLA. Because these reactions are reported voluntarily from a population of uncertain size, it is not always possible to reliably estimate their frequency or establish a causal relationship to drug exposure.

Adverse Reactions from Observational Studies

- CHF and > 10% reduction in LVEF in patients with HER2-positive metastatic breast cancer with a baseline LVEF of 40-49% treated with KADCYLA [see Warnings and Precautions (5.2)].

Adverse Reactions from Postmarketing Spontaneous Reports

- Tumor lysis syndrome (TLS)
- Skin/tissue necrosis after extravasation

7 DRUG INTERACTIONS

No formal drug-drug interaction studies with KADCYLA have been conducted. In vitro studies indicate that DM1, the cytotoxic component of KADCYLA, is metabolized mainly by CYP3A4 and to a lesser extent by CYP3A5. Concomitant use of strong CYP3A4 inhibitors (e.g., ketoconazole, itraconazole, clarithromycin, atazanavir, indinavir, nefazodone, nelfinavir, ritonavir, saquinavir, telithromycin, and voriconazole) with KADCYLA should be avoided due to the potential for an increase in DM1 exposure and toxicity. Consider an alternate medication with no or minimal potential to inhibit CYP3A4. If concomitant use of strong CYP3A4 inhibitors is unavoidable, consider delaying KADCYLA treatment until the strong CYP3A4 inhibitors have cleared from the circulation (approximately 3 elimination half-lives of the inhibitors) when possible. If a strong CYP3A4 inhibitor is coadministered and KADCYLA treatment cannot be delayed, patients should be closely monitored for adverse reactions.

8 USE IN SPECIFIC POPULATIONS

8.1 Pregnancy

If KADCYLA is administered during pregnancy, or if a patient becomes pregnant while receiving KADCYLA or within 7 months following the last dose of KADCYLA, health care providers and patients should immediately report KADCYLA exposure to Genentech at 1-888-835-2555.

Risk Summary

KADCYLA can cause fetal harm when administered to a pregnant woman. There are no available data on the use of KADCYLA in pregnant women. Cases of oligohydramnios and oligohydramnios sequence manifesting as pulmonary hypoplasia, skeletal abnormalities, and neonatal death were observed in the postmarketing setting in patients treated with trastuzumab, the antibody component of KADCYLA [see Data]. Based on its mechanism of action, the DM1 component of KADCYLA can also cause embryo-fetal harm when administered to a pregnant woman [see Data]. Apprise the patient of the potential risks to a fetus. There are clinical considerations if KADCYLA is used in a pregnant woman, or if a patient becomes pregnant within 7 months following the last dose of KADCYLA [see Clinical Considerations].

The estimated background risk of major birth defects and miscarriage for the indicated population is unknown. In the U.S. general population, the estimated background risk of major birth defects and miscarriage in clinically recognized pregnancies is 2-4% and 15-20%, respectively.

Clinical Considerations

Fetal/Neonatal Adverse Reactions

Monitor women who received KADCYLA during pregnancy or within 7 months prior to conception for oligohydramnios. If oligohydramnios occurs, perform fetal testing that is appropriate for gestational age and consistent with community standards of care.

Data

Human Data

There are no available data on the use of KADCYLA in pregnant women. In the post-marketing setting, cases of oligohydramnios, and of oligohydramnios sequence, manifesting in the fetus as pulmonary hypoplasia, skeletal abnormalities and neonatal death were observed after treatment with trastuzumab during pregnancy. These case reports described oligohydramnios in pregnant women who received trastuzumab either alone or in combination with chemotherapy. In some case reports, amniotic fluid index increased after trastuzumab was stopped. In one case, trastuzumab therapy resumed after amniotic index improved, and oligohydramnios recurred.

Animal Data

There were no reproductive and developmental toxicology studies conducted with ado-trastuzumab emtansine. DM1, the cytotoxic component of KADCYLA, disrupts microtubule function. DM1 is toxic to rapidly dividing cells in animals and is genotoxic, suggesting it has the potential to cause embryotoxicity and teratogenicity. In studies where trastuzumab was administered to pregnant cynomolgus monkeys during the period of organogenesis at doses up to 25 mg/kg given twice weekly (about 7 times the clinical dose), trastuzumab crossed the placental barrier during the early (Gestation Days 20 to 50) and late (Gestation Days 120 to 150) phases of gestation. The resulting concentrations of trastuzumab in fetal serum and amniotic fluid were approximately 33% and 25%, respectively, of those present in the maternal serum but were not associated with adverse developmental effects.

8.2 Lactation

Risk Summary

There is no information regarding the presence of ado-trastuzumab emtansine in human milk, the effects on the breastfed infant, or the effects on milk production. DM1, the cytotoxic component of KADCYLA, may cause serious adverse reactions in breastfed infants based on its mechanism of action [see Data]. Advise women not to breastfeed during treatment and for 7 months following the last dose of KADCYLA.

Data

There were no animal lactation studies conducted with ado-trastuzumab emtansine or the cytotoxic component of KADCYLA (DM1). In lactating cynomolgus monkeys, trastuzumab was present in breast milk at about 0.3% of maternal serum concentrations after pre- (beginning Gestation Day 120) and post-partum (through Post-partum Day 28) doses of 25 mg/kg administered twice weekly (about 7 times the clinical dose of KADCYLA). Infant monkeys with detectable serum levels of trastuzumab did not exhibit any adverse effects on growth or development from birth to 1 month of age.

8.3 Females and Males of Reproductive Potential

Pregnancy Testing

Verify the pregnancy status of females of reproductive potential prior to the initiation of KADCYLA.

Contraception

Females

KADCYLA can cause embryo-fetal harm when administered during pregnancy. Advise females of reproductive potential to use effective contraception during treatment and for 7 months following the last dose of KADCYLA [see Use in Specific Populations (8.1)].

Males

Because of the potential for genotoxicity, advise male patients with female partners of reproductive potential to use effective contraception during treatment with KADCYLA and for 4 months following the last dose.

Infertility

Based on results from animal toxicity studies, KADCYLA may impair fertility in females and males of reproductive potential. It is not known if the effects are reversible [see Nonclinical Toxicology (13.1)].

8.4 Pediatric Use

Safety and effectiveness of KADCYLA have not been established in pediatric patients.

8.5 Geriatric Use

Of the 495 patients who were randomized to KADCYLA in EMILIA [see Clinical Studies (14.1)], 65 patients (13%) were ≥ 65 years of age and 11 patients (2%) were ≥ 75 years of age. In patients ≥ 65 years old (n=138 across both treatment arms) the hazard ratios for progression-free survival (PFS) and overall survival (OS) were 1.06 (95% CI: 0.68, 1.66) and 1.05 (95% CI: 0.58, 1.91), respectively. No overall differences in the safety of KADCYLA were observed in patients aged ≥ 65 compared to patients < 65 years of age. EMILIA did not include sufficient numbers of patients aged ≥ 75 years to draw conclusions on the safety or effectiveness of KADCYLA in this age group.

Of the 743 patients who were randomized to KADCYLA in KATHERINE [see Clinical Studies (14.2)], 58 patients (8%) were ≥ 65 years of age and 2 patients (0.3%) were ≥ 75 years of age. No overall differences in the safety or effectiveness of KADCYLA were observed in patients aged ≥ 65 compared to patients < 65 years of age. KATHERINE did not include sufficient numbers of patients aged ≥ 75 years to draw conclusions on the safety or effectiveness of KADCYLA in this age group.

Population pharmacokinetic analysis indicates that age does not have a clinically meaningful effect on the pharmacokinetics of ado-trastuzumab emtansine [see Clinical Pharmacology (12.3)].

8.6 Renal Impairment

No dedicated renal impairment trial for KADCYLA has been conducted. Based on the population pharmacokinetics, as well as analysis of Grade 3 or greater adverse reactions and dose modifications, dose adjustments of KADCYLA are not needed in patients with mild (creatinine clearance [CLcr] 60 to 89 mL/min) or moderate (CLcr 30 to 59 mL/min) renal impairment. No dose adjustment can be recommended for patients with severe renal impairment (CLcr less than 30 mL/min) because of the limited data available [see Clinical Pharmacology (12.3)].

8.7 Hepatic Impairment

No adjustment to the starting dose is required for patients with mild or moderate hepatic impairment [see Clinical Pharmacology (12.3)]. KADCYLA was not studied in patients with severe hepatic impairment. Closely monitor patients with hepatic impairment due to known hepatotoxicity observed with KADCYLA [see Warnings and Precautions, Hepatotoxicity (5.1)].

10 OVERDOSAGE

There is no known antidote for overdose of KADCYLA. In clinical trials, overdose of KADCYLA has been reported at approximately two times the recommended dose which resulted in Grade 2 thrombocytopenia (resolved 4 days later) and one death. In the fatal case, the patient incorrectly received KADCYLA at 6 mg/kg and died approximately 3 weeks following the overdose; a cause of death and a causal relationship to KADCYLA were not established.

11 DESCRIPTION

KADCYLA (ado-trastuzumab emtansine) is a HER2-targeted antibody-drug conjugate (ADC) which contains the humanized anti-HER2 IgG1, trastuzumab, covalently linked to the microtubule inhibitory drug DM1 (a maytansine derivative) via the stable thioether linker MCC (4-[N-maleimidomethyl] cyclohexane-1-carboxylate). Emtansine refers to the MCC-DM1 complex.

The antibody trastuzumab, is a well characterized recombinant monoclonal antibody product produced by mammalian (Chinese hamster ovary) cells, and the small molecule components (DM1 and MCC) are produced by chemical synthesis. Ado-trastuzumab emtansine contains an average of 3.5 DM1 molecules per antibody. Ado-trastuzumab emtansine has the following chemical structure:

Note: The bracketed structure is DM1 plus MCC which represents the emtansine component. The n is, on average, 3.5 DM1 molecules per trastuzumab (Mab) molecule.

KADCYLA (ado-trastuzumab emtansine) is a sterile, white to off-white preservative free lyophilized powder in single-dose vials. Each vial contains 100 mg or 160 mg ado-trastuzumab emtansine. Following reconstitution, each single-dose vial contains ado-trastuzumab emtansine (20 mg/mL), polysorbate 20 [0.02% (w/v)], sodium succinate (10 mM), and sucrose [6% (w/v)] with a pH of 5.0. The resulting solution containing 20 mg/mL ado-trastuzumab emtansine is administered by intravenous infusion following dilution.

12 CLINICAL PHARMACOLOGY

12.1 Mechanism of Action

Ado-trastuzumab emtansine is a HER2-targeted antibody-drug conjugate. The antibody is the humanized anti-HER2 IgG1, trastuzumab. The small molecule cytotoxin, DM1, is a microtubule inhibitor. Upon binding to sub-domain IV of the HER2 receptor, ado-trastuzumab emtansine undergoes receptor-mediated internalization and subsequent lysosomal degradation, resulting in intracellular release of DM1-containing cytotoxic catabolites. Binding of DM1 to tubulin disrupts microtubule networks in the cell, which results in cell cycle arrest and apoptotic cell death. In addition, in vitro studies have shown that similar to trastuzumab, ado-trastuzumab emtansine inhibits HER2 receptor signaling, mediates antibody-dependent cell-mediated cytotoxicity and inhibits shedding of the HER2 extracellular domain in human breast cancer cells that overexpress HER2.

12.2 Pharmacodynamics

Cardiac Electrophysiology

The effect of multiple doses of KADCYLA (3.6 mg/kg every 3 weeks) on the QTc interval was evaluated in an open label, single arm study in 51 patients with HER2-positive metastatic breast cancer. No large changes in the mean QT interval (i.e., > 20 ms) were detected in the study.

12.3 Pharmacokinetics

The pharmacokinetics of KADCYLA was evaluated in a phase 1 study and in a population pharmacokinetic analysis for the ado-trastuzumab emtansine conjugate (ADC) using pooled data from 5 trials in patients with breast cancer. A linear two-compartment model with first-order elimination from the central compartment adequately describes the ADC concentration-time profile. In addition to ADC, the pharmacokinetics of total antibody (conjugated and unconjugated trastuzumab), DM1 were also determined. The population pharmacokinetic analysis of ADC suggested no difference in KADCYLA exposure based on disease status (adjuvant vs. metastatic setting). The pharmacokinetics of KADCYLA are summarized below.

Distribution

Maximum concentrations (Cmax) of ADC and DM1 were observed close to the end of infusion. In EMILIA, mean (SD) ADC and DM1 Cycle 1 Cmax following KADCYLA administration was 83.4 (16.5) µg/mL and 4.61 (1.61) ng/mL, respectively. In KATHERINE, mean (SD) ADC and DM1 Cycle 1 Cmax following KADCYLA administration was 72.6 (24.3) µg/mL and 4.71 (2.25) ng/mL, respectively.

In vitro, the mean binding of DM1 to human plasma proteins was 93%. In vitro, DM1 was a substrate of P-glycoprotein (P-gp).

Based on population pharmacokinetic analysis, the central volume of distribution of ADC was 3.13 L.

Metabolism

In vitro studies indicate that DM1, the small molecule component of KADCYLA, undergoes metabolism by CYP3A4/5. DM1 did not inhibit or induce major CYP450 enzymes in vitro. In human plasma, ado-trastuzumab emtansine catabolites MCC-DM1, Lys-MCC-DM1, and DM1 were detected at low levels.

Elimination

Based on population pharmacokinetic analysis, following intravenous infusion of KADCYLA, the clearance of the ADC was 0.68 L/day and the elimination half-life (t1/2) was approximately 4 days. No accumulation of KADCYLA was observed after repeated dosing of intravenous infusion every 3 weeks.

Based on population pharmacokinetic analysis (n=671), body weight, sum of longest diameter of target lesions by RECIST, HER2 extracellular domain (ECD) concentrations, AST, albumin, and baseline trastuzumab concentrations were identified as statistically significant covariates for ado-trastuzumab emtansine clearance. However, the magnitude of effect of these covariates on ado-trastuzumab emtansine exposure suggests that, with the exception of body weight, these covariates are unlikely to have a clinically meaningful effect on KADCYLA exposure. Therefore, the body weight based dose of 3.6 mg/kg every 3 weeks without correction for other covariates is considered appropriate.

Effect of Renal Impairment

Based on population pharmacokinetic analysis in 668 patients, including moderate (CLcr 30 - 59 mL/min, n=53) and mild (CLcr 60 - 89 mL/min, n=254) renal impairment, indicate that pharmacokinetics of the ADC is not affected by mild to moderate renal impairment as compared to normal renal function (CLcr ≥ 90 mL/min, n=361). Data from only one patient with severe renal impairment (CLcr < 30 mL/min) is available [see Use in Specific Populations (8.7)].

Effect of Hepatic Impairment

The liver is a primary organ for eliminating DM1 and DM1-containing catabolites. The pharmacokinetics of ado-trastuzumab emtansine and DM1-containing catabolites were evaluated after the administration of 3.6 mg/kg of KADCYLA to metastatic HER2-positive breast cancer patients with normal hepatic function (n=10), mild (Child-Pugh A; n=10) and moderate (Child-Pugh B; n=8) hepatic impairment.

- Plasma concentrations of DM1 and DM1-containing catabolites (Lys-MCC-DM1 and MCC-DM1) were low and comparable between patients with and without hepatic impairment.
- Systemic exposures (AUC) of ado-trastuzumab emtansine at Cycle 1 in patients with mild and moderate hepatic impairment were approximately 38% and 67% lower than that of patients with normal hepatic function, respectively. Ado-trastuzumab emtansine exposure (AUC) at Cycle 3 after repeated dosing in patients with mild or moderate hepatic dysfunction was within the range observed in patients with normal hepatic function.

KADCYLA has not been studied in patients with severe hepatic impairment (Child-Pugh class C).

Effects of Age and Race

Based on population pharmacokinetic analysis, age (< 65 [n=577]; 65 - 75 (n=78); > 75 [n=16]) and race (Asian [n=73]; non-Asian [n=598]) do not have a clinically meaningful effect on the pharmacokinetics of ado-trastuzumab emtansine.

12.6 Immunogenicity

The observed incidence of anti-drug antibodies (ADA) is highly dependent on the sensitivity and specificity of the assay. Differences in assay methods preclude meaningful comparisons of the incidence of ADA in the studies described below with the incidence of ADA in other studies, including those of ado-trastuzumab emtansine or of other ado-trastuzumab emtansine products.

Among patients who received KADCYLA as a single agent for a median duration of 10 months in seven clinical trials, 5% (64/1243) of patients tested positive for antibodies against ado-trastuzumab emtansine at one or more post-dose timepoints. Neutralizing antibodies against ado-trastuzumab emtansine were detected in 45% (18/40) of evaluable patients who were ADA positive. Because of the low occurrence of ADA, the effect of these antibodies on the pharmacokinetics, pharmacodynamics, safety, and/or effectiveness of ado-trastuzumab emtansine is unknown. The presence of ado-trastuzumab emtansine in patient serum at the time of ADA sampling may interfere with the ability of this assay to detect anti-ado-trastuzumab emtansine antibodies. As a result, data may not accurately reflect the true incidence of anti-ado-trastuzumab emtansine antibody development.

13 NONCLINICAL TOXICOLOGY

13.1 Carcinogenesis, Mutagenesis, Impairment of Fertility

Carcinogenicity studies have not been conducted with ado-trastuzumab emtansine.

DM1 was aneugenic or clastogenic in an in vivo single-dose rat bone marrow micronucleus assay at exposures that were comparable to mean maximum concentrations of DM1 measured in humans administered KADCYLA. DM1 was not mutagenic in an in vitro bacterial reverse mutation (Ames) assay.

Based on results from animal toxicity studies, KADCYLA may impair fertility in humans. In a single-dose toxicity study of ado-trastuzumab emtansine in rats, degeneration of seminiferous tubules with hemorrhage in the testes associated with increased weights of testes and epididymides at a severely toxic dose level (60 mg/kg; about 4 times the clinical exposure based on AUC) were observed. The same dose in female rats resulted in signs of hemorrhage and necrosis of the corpus luteum in ovaries. In monkeys dosed with ado-trastuzumab emtansine once every three weeks for 12 weeks (four doses), at up to 30 mg/kg (about 7 times the clinical exposure based on AUC), there were decreases in the weights of epididymides, prostate, testes, seminal vesicles and uterus, although the interpretation of these effects is unclear due to the varied sexual maturity of enrolled animals.

13.2 Animal Toxicology and/or Pharmacology

In monkeys, treatment with doses of ado-trastuzumab emtansine up to 30 mg/kg (about 7 times the clinical exposure based on AUC) caused dose dependent axonal degeneration in the sciatic nerve with hypertrophy or hyperplasia of the Schwann cells, and axonal degeneration of the dorsal funiculus in the spinal cord. Based on the mechanism of action of the cytotoxic component DM1, there is clinical potential for neurotoxicity [see Warnings and Precautions (5.8)].

14 CLINICAL STUDIES

14.1 Metastatic Breast Cancer

The efficacy of KADCYLA was evaluated in a randomized, multicenter, open-label trial (EMILIA) (NCT00829166) of 991 patients with HER2-positive, unresectable locally advanced or metastatic breast cancer. Prior taxane and trastuzumab-based therapy was required before trial enrollment. Patients with only prior adjuvant therapy were required to have disease recurrence during or within six months of completing adjuvant therapy. Breast tumor samples were required to show HER2 overexpression defined as 3+ IHC or FISH amplification ratio ≥ 2.0 determined at a central laboratory. Patients were randomly allocated (1:1) to receive lapatinib plus capecitabine or KADCYLA. Randomization was stratified by world region (United States, Western Europe, other), number of prior chemotherapy regimens for unresectable locally advanced or metastatic disease (0–1, > 1) and visceral versus non-visceral disease as determined by the investigators.

KADCYLA was given intravenously at 3.6 mg/kg on Day 1 of a 21-day cycle. Lapatinib was administered at 1250 mg/day orally once per day of a 21-day cycle and capecitabine was administered at 1000 mg/m^2 orally twice daily on Days 1−14 of a 21-day cycle. Patients were treated with KADCYLA or lapatinib plus capecitabine until progression of disease, withdrawal of consent, or unacceptable toxicity. At the time of the primary analysis, median time on study drug was 5.7 months (range: 0–28.4) for KADCYLA, 4.9 months (range: 0–30.8) for lapatinib, and 4.8 months (range: 0–30.4) for capecitabine.

The co-primary efficacy outcomes of the study were progression-free survival (PFS) based on tumor response assessments by an independent review committee (IRC), and overall survival (OS). PFS was defined as the time from the date of randomization to the date of disease progression or death from any cause (whichever occurred earlier). Overall survival was defined as the time from the date of randomization to the date of death from any cause. Additional outcomes included PFS (based on investigator tumor response assessments), objective response rate (ORR), duration of response and time to symptom progression.

Patient demographics and baseline tumor characteristics were balanced between treatment arms. All patients had metastatic disease at study entry. The median age was approximately 53 years (range 24-84 years), 74% were White, 18% were Asian and 5% were Black. All but 5 patients were women. Twenty-seven percent of patients were enrolled in United States, 32% in Europe and 16% in Asia. Tumor prognostic characteristics including hormone receptor status (positive: 55%, negative: 43%), presence of visceral disease (68%) and non-visceral disease only (33%) and the number of metastatic sites (< 3: 61%, ≥ 3: 37%) were similar in the study arms.

The majority of patients (88%) had received prior systemic treatment in the metastatic setting. Twelve percent of patients had prior treatment only in the neoadjuvant or adjuvant setting and had disease relapse within 6 months of treatment. All but one patient received trastuzumab prior to study entry; approximately 85% of patients received prior trastuzumab in the metastatic setting. Over 99% percent of patients had received a taxane, and 61% of patients had received an anthracycline prior to study entry. Overall, patients received a median of 3 systemic agents in the metastatic setting. Among patients with hormone receptor-positive tumors, 44.4% received prior adjuvant hormonal therapy and 44.8% received hormonal therapy for locally advanced/metastatic disease.

The randomized trial demonstrated a statistically significant improvement in IRC-assessed PFS in the KADCYLA-treated group compared with the lapatinib plus capecitabine-treated group [hazard ratio (HR) = 0.65, 95% CI: 0.55, 0.77, p < 0.0001], and an increase in median PFS of 3.2 months (median PFS of 9.6 months in the KADCYLA-treated group vs. 6.4 months in the lapatinib plus capecitabine group). See Table 7 and Figure 1. The results for investigator-assessed PFS were similar to those observed for IRC-assessed PFS.

At the time of PFS analysis, 223 patients had died. More deaths occurred in the lapatinib plus capecitabine arm (26%) compared with the KADCYLA arm (19%), however the results of this interim OS analysis did not meet the pre-specified stopping boundary for statistical significance. At the time of the second interim OS analysis, 331 events had occurred. The co-primary endpoint of OS was met; OS was significantly improved in patients receiving KADCYLA (HR = 0.68, 95% CI: 0.55, 0.85, p = 0.0006). This result crossed the pre-specified efficacy stopping boundary (HR = 0.73 or p = 0.0037). The median duration of survival was 30.9 months in the KADCYLA arm vs. 25.1 months in the lapatinib plus capecitabine arm. See Table 7 and Figure 2.

A treatment benefit with KADCYLA in terms of PFS and OS was observed in patient subgroups based on stratification factors, key baseline demographic and disease characteristics, and prior treatments. In the subgroup of patients with hormone receptor-negative disease (n=426), the hazard ratios for PFS and OS were 0.56 (95% CI: 0.44, 0.72) and 0.75 (95% CI: 0.54, 1.03), respectively. In the subgroup of patients with hormone receptor-positive disease (n=545), the hazard ratios for PFS and OS were 0.72 (95% CI: 0.58, 0.91) and 0.62 (95% CI: 0.46, 0.85), respectively. In the subgroup of patients with non-measurable disease (n=205), based on IRC assessments, the hazard ratios for PFS and OS were 0.91 (95% CI: 0.59, 1.42) and 0.96 (95% CI: 0.54, 1.68), respectively; in patients with measurable disease the hazard ratios were 0.62 (95% CI: 0.52, 0.75) and 0.65 (95% CI: 0.51, 0.82), respectively. The PFS and OS hazard ratios in patients who were younger than 65 years old (n=853) were 0.62 (95% CI: 0.52, 0.74) and 0.66 (95% CI: 0.52, 0.83), respectively. In patients ≥ 65 years old (n=138), the hazard ratios for PFS and OS were 1.06 (95% CI: 0.68, 1.66) and 1.05 (95% CI: 0.58, 1.91), respectively.

Table 7 Summary of Efficacy from EMILIA
 | KADCYLA N=495 | Lapatinib+Capecitabine N=496
Progression-Free Survival (independent review)
Number (%) of patients with event | 265 (53.5%) | 304 (61.3%)
Median duration of PFS (months) | 9.6 | 6.4
Hazard Ratio (stratified [Stratified by world region (United States, Western Europe, other), number of prior chemotherapeutic regimens for locally advanced or metastatic disease (0-1 vs. > 1), and visceral vs. non-visceral disease.]) | 0.650
95% CI for Hazard Ratio | (0.549, 0.771)
p-value (Log-Rank test, stratified) | < 0.0001
Overall Survival [The second interim analysis for OS was conducted when 331 events were observed and the results are presented in this table.]
Number (%) of patients who died | 149 (30.1%) | 182 (36.7%)
Median duration of survival (months) | 30.9 | 25.1
Hazard Ratio (stratified) | 0.682
95% CI for Hazard Ratio | (0.548, 0.849)
p-value (Log-Rank test) | 0.0006
Objective Response Rate (independent review)
Patients with measurable disease | 397 | 389
Number of patients with OR (%) | 173 (43.6%) | 120 (30.8%)
Difference (95% CI) | 12.7% (6.0, 19.4)
Duration of Objective Response (months)
Number of patients with OR | 173 | 120
Median duration (95% CI) | 12.6 (8.4, 20.8) | 6.5 (5.5, 7.2)
PFS: progression-free survival; OR: objective response

Figure 1 Kaplan-Meier Curve of IRC-Assessed Progression-Free Survival for EMILIA

Figure 2 Kaplan-Meier Curve of Overall Survival for EMILIA

14.2 Early Breast Cancer

KATHERINE (NCT01772472) was a randomized, multicenter, open-label trial of 1486 patients with HER2-positive, early breast cancer. Patients were required to have had neoadjuvant taxane and trastuzumab-based therapy with residual invasive tumor in the breast and/or axillary lymph nodes. Patients received radiotherapy and/or hormonal therapy concurrent with study treatment as per local guidelines. Breast tumor samples were required to show HER2 overexpression defined as 3+ IHC or ISH amplification ratio ≥ 2.0 determined at a central laboratory using Ventana's PATHWAY anti-HER2-/neu (4B5) Rabbit Monoclonal Primary Antibody or INFORM HER2 Dual ISH DNA Probe Cocktail assays. Patients were randomized (1:1) to receive KADCYLA or trastuzumab. Randomization was stratified by clinical stage at presentation, hormone receptor status, preoperative HER2-directed therapy (trastuzumab, trastuzumab plus additional HER2-directed agent[s]), and pathological nodal status evaluation after preoperative therapy.

KADCYLA was given intravenously at 3.6 mg/kg on Day 1 of a 21-day cycle. Trastuzumab was given intravenously at 6 mg/kg on Day 1 of a 21-day cycle. Patients were treated with KADCYLA or trastuzumab for a total of 14 cycles unless there was recurrence of disease, withdrawal of consent, or unacceptable toxicity. At the time of the major efficacy outcome analysis, median treatment duration was 10 months for both KADCYLA- and trastuzumab-treated patients. Patients who discontinued KADCYLA for reasons other than disease recurrence could complete the remainder of the planned HER2-directed therapy with trastuzumab if appropriate based on toxicity considerations and investigator discretion.

The major efficacy outcome of the study was invasive disease-free survival (IDFS). IDFS was defined as the time from the date of randomization to first occurrence of ipsilateral invasive breast tumor recurrence, ipsilateral local or regional invasive breast cancer recurrence, distant recurrence, contralateral invasive breast cancer, or death from any cause. Additional efficacy outcomes included IDFS including second primary non-breast cancer, disease free survival (DFS), and overall survival (OS).

Patient demographics and baseline tumor characteristics were generally balanced between treatment arms. The median age was approximately 49 years (range 23-80 years), 73% were White, 9% were Asian, 6% were American Indian or Alaska Native and 3% were Black or African American. Most patients (99.7%) were women. Enrollment by region was as follows: 23% in North America, 54% in Europe and 23% throughout the rest of the world. Tumor prognostic characteristics including hormone receptor status (positive: 72%, negative: 28%), clinical stage at presentation (inoperable: 25%, operable: 75%) and pathological nodal status after preoperative therapy (node positive: 46%, node negative or not evaluated: 54%) were similar across study arms.

The majority of patients (77%) had received an anthracycline-containing neoadjuvant chemotherapy regimen. Twenty percent of patients received another HER2-targeted agent in addition to trastuzumab as a component of neoadjuvant therapy; 94% of these patients received pertuzumab.

A statistically significant improvement in IDFS and OS was observed in patients who received KADCYLA compared with trastuzumab.

The efficacy results from KATHERINE are summarized in Table 8, Figure 3, and Figure 4.

Table 8 Efficacy Results from KATHERINE
 | KADCYLA N=743 | Trastuzumab N=743
Invasive Disease-Free Survival (IDFS) [Hierarchical testing applied for IDFS and OS] , [Data from the pre-specified interim analysis of IDFS (67% of the number of events for the planned final analysis) with the p-value compared with the allocated alpha of 0.012]
Number (%) of patients with event | 91 (12.2%) | 165 (22.2%)
HR [95% CI] [Unstratified analysis] | 0.50 [0.39, 0.64]
p-value (Log-Rank test, unstratified) | < 0.0001
3-year event-free rate [3-year event-free rate derived from Kaplan-Meier estimates] , % [95% CI] | 88.3 [85.8, 90.7] | 77.0 [73.8, 80.7]
Overall Survival (OS), [Data from the pre-specified second interim analysis of OS (82% of the number of events for the planned final analysis) with the p-value compared with the allocated alpha of 0.0263 based on the actual number of OS events at the time of the analysis]
Number (%) of patients with event | 89 (12.0%) | 126 (17.0%)
HR [95% CI] | 0.66 [0.51, 0.87]
p-value (Log-Rank test, unstratified) | 0.0027
IDFS including second primary non-breast cancer
Number (%) of patients with event | 95 (12.8%) | 167 (22.5%)
HR [95% CI] | 0.51 [0.40, 0.66]
3-year event-free rate, % [95% CI] | 87.7 [85.2, 90.2] | 76.9 [73.7, 80.1]
Disease-Free Survival (DFS)
Number (%) of patients with event | 98 (13.2%) | 167 (22.5%)
HR [95% CI] | 0.53 [0.41, 0.68]
3-year event-free rate, % [95% CI] | 87.4 [84.9, 89.9] | 76.9 [73.7, 80.1]
HR: Hazard Ratio; CI: Confidence Intervals,

Figure 3 Kaplan-Meier Curve of Invasive Disease-Free Survival in KATHERINE

Figure 4 Kaplan-Meier Curve of Overall Survival in KATHERINE

15 REFERENCES

1. OSHA Hazardous Drugs. OSHA. http://www.osha.gov/SLTC/hazardousdrugs/index.html

16 HOW SUPPLIED/STORAGE AND HANDLING

16.1 How Supplied/Storage

KADCYLA (ado-trastuzumab emtansine) is supplied as:

Carton Contents | NDC
One 100 mg vial, single-dose vial | NDC 50242-088-01
One 160 mg vial, single-dose vial | NDC 50242-087-01

Store vials in a refrigerator at 2°C to 8°C (36°F to 46°F) until time of reconstitution. Do not freeze or shake.

16.2 Special Handling

Follow procedures for proper handling and disposal of anticancer drugs.

17 PATIENT COUNSELING INFORMATION

Hepatotoxicity

- Inform patients of the possibility of severe liver injury and advise patients to immediately seek medical attention if they experience symptoms of acute hepatitis such as nausea, vomiting, abdominal pain (especially RUQ abdominal pain), jaundice, dark urine, generalized pruritus, anorexia, etc. [see Warnings and Precautions (5.1)].

Left Ventricular Dysfunction

- Advise patients to contact a health care professional immediately for any of the following: new onset or worsening shortness of breath, cough, swelling of the ankles/legs, palpitations, weight gain of more than 5 pounds in 24 hours, dizziness or loss of consciousness [see Warnings and Precautions (5.2)].

Embryo-Fetal Toxicity

- Advise pregnant women and females of reproductive potential that KADCYLA exposure during pregnancy or within 7 months prior to conception can result in fetal harm. Advise female patients to contact their healthcare provider with a known or suspected pregnancy [see Use in Specific Populations (8.1, 8.3)].
- Encourage women who are exposed to KADCYLA during pregnancy or who become pregnant within 7 months following the last dose of KADCYLA to report their pregnancy to Genentech [see Use in Specific Populations (8.1)].
- Advise females of reproductive potential to use effective contraception during treatment and for 7 months following the last dose of KADCYLA [see Use in Specific Populations (8.1, 8.3)].
- Advise male patients with female partners of reproductive potential to use effective contraception during treatment and for 4 months following the last dose of KADCYLA [see Use in Specific Populations (8.3)].

Lactation

- Advise women not to breastfeed during treatment and for 7 months after the last dose of KADCYLA [see Use in Specific Populations (8.2)].

KADCYLA® [ado-trastuzumab emtansine]

Manufactured by:
Genentech, Inc.
A Member of the Roche Group
1 DNA Way
South San Francisco, CA 94080-4990
U.S. License No: 1048

KADCYLA is a trademark of Genentech, Inc.
©2025 Genentech, Inc.

Representative sample of labeling (see the HOW SUPPLIED section for complete listing):

PRINCIPAL DISPLAY PANEL - 100 mg Vial Carton

NDC 50242-088-01

Kadcyla®
(ado-trastuzumab
emtansine)
For Injection

100 mg per vial

For Intravenous Infusion Only
Reconstitute and Dilute prior
to administration
Single-Dose Vial –
Discard Unused Portion

KEEP REFRIGERATED

Rx only

1 vial

Genentech

10217212

PRINCIPAL DISPLAY PANEL - 160 mg Vial Carton

NDC 50242-087-01

Kadcyla®
(ado-trastuzumab
emtansine)
For Injection

160 mg per vial

For Intravenous Infusion Only
Reconstitute and Dilute prior
to administration
Single-Dose Vial –
Discard Unused Portion

KEEP REFRIGERATED

Rx only

1 vial

Genentech

10217217